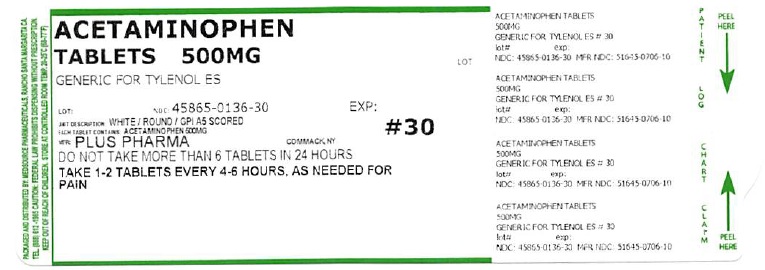 DRUG LABEL: Acetaminophen
NDC: 45865-136 | Form: TABLET
Manufacturer: Medsouce Pharmaceuticals
Category: otc | Type: HUMAN OTC DRUG LABEL
Date: 20201005

ACTIVE INGREDIENTS: ACETAMINOPHEN 500 mg/1 1
INACTIVE INGREDIENTS: POVIDONE; STARCH, CORN; SODIUM STARCH GLYCOLATE TYPE A CORN; STEARIC ACID

Acetaminophen 500 mg Tablet

Active ingredient (in each tablet)

Acetaminophen 500 mg

Purposes

Pain reliever/fever reducer

Uses

- for the temporary relief of minor aches and pains due to:

- headache
- muscular aches
- backache
- minor pain of arthritis
- the common cold
- toothache
- premenstrual and menstrual cramps
- temporarily reduces fever

Warnings

Liver warning: This product contains acetaminophen. The maximum daily dose of this product is 6 tablets (3,000 mg) in 24 hours. Severe liver damage may occur if you take

- more than 4,000 mg of acetaminophen in 24 hours
- with other drugs containing acetaminophen
- 3 or more alcoholic drinks every day while using this product

Do not use

- with any other drug containing acetaminophen (prescription or non prescription). If you are not sure whether a drug contains acetaminophen, ask a doctor or pharmacist.
- if you are allergic to acetaminophen or any of the inactive ingredients in this product

Ask a doctor before use if you have

liver disease.

Ask a doctor or pharmacist before use if you are

taking the blood thinning drug warfarin.

Stop use and ask a doctor if

- pain gets worse or lasts more than 10 days
- fever gets worse or lasts more than 3 days
- new symptoms occur
- redness or swelling is present

These could be signs of a serious condition.

PREGNANCY OR BREAST FEEDING

If pregnant or breast-feeding, ask a health professional before use.

Keep out of reach of children.

Overdose Warning: Taking more than the recommended dose (overdose) may cause liver damage. In the case of overdose, get medical help or contact a Poison Control Center right away (1-800-222-1222). Quick medical attention is critical for adults as well as for children even if you do not notice any signs or symptoms.

Directions

Do not take more than directed (see overdose warning)
Adults and children 12 years and over:

- take 2 tablets every 6 hours while symptoms last
- do not take more than 6 tablets in 24 hours unless directed by a doctor
- do not take for more than 10 days unless directed by a doctor.

Children under 12 years: ask a doctor.

Other information

- Do not use if imprinted safety seal under cap is broken or missing
- Store at room temperature

Inactive ingredients

Povidone, Pregelatinized Starch, Sodium Starch Glycolate, Stearic Acid.

Questions?

If you have any questions or comments, or to report an adverse event, please contact (800) 795-9775.